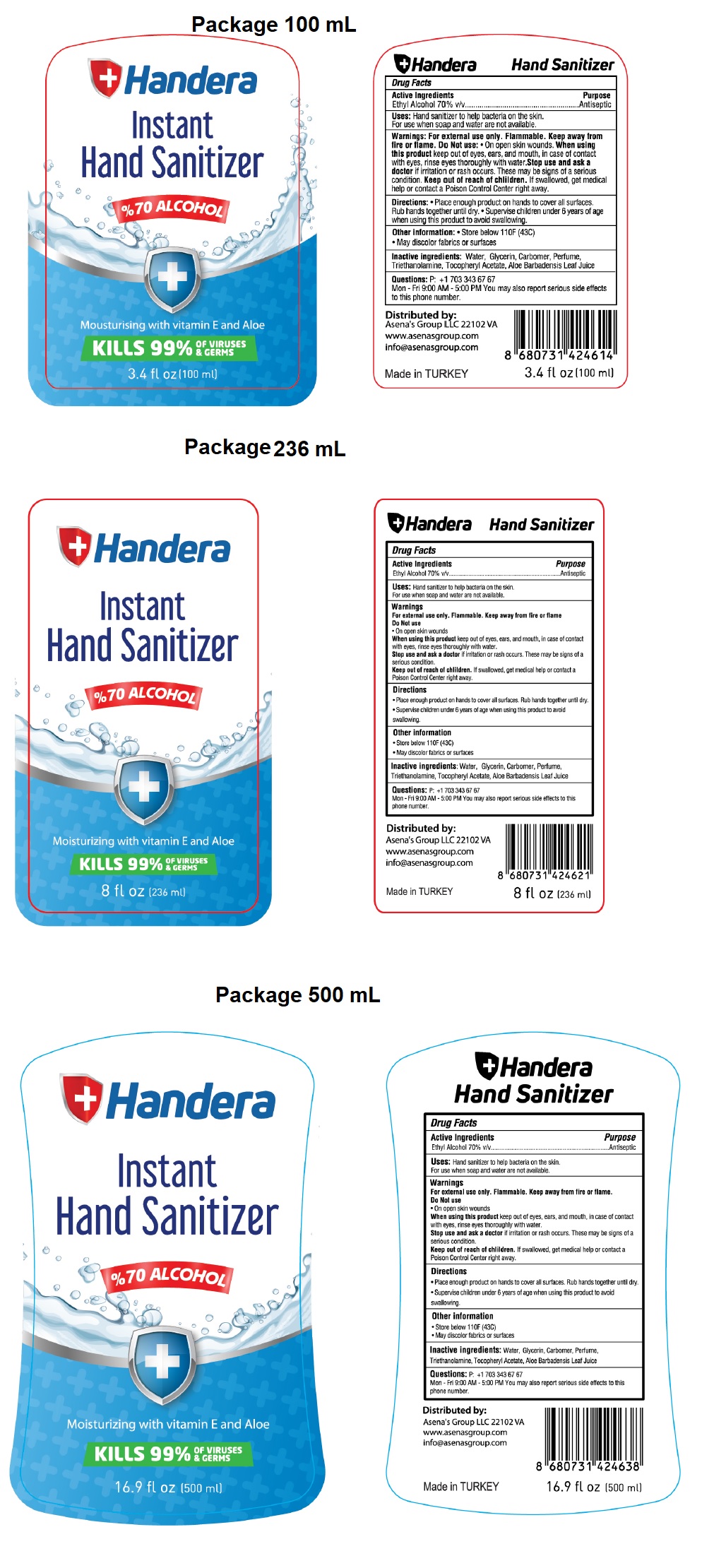 DRUG LABEL: Handera Instant Hand Sanitizer
NDC: 78089-027 | Form: SOLUTION
Manufacturer: Endeks Kimya Sanayi Ve Ticaret Anonim Sirketi
Category: otc | Type: HUMAN OTC DRUG LABEL
Date: 20200625

ACTIVE INGREDIENTS: ALCOHOL 70 mL/100 mL
INACTIVE INGREDIENTS: WATER; GLYCERIN; CARBOMER HOMOPOLYMER, UNSPECIFIED TYPE; TROLAMINE; .ALPHA.-TOCOPHEROL ACETATE; ALOE VERA LEAF

Handera Instant Hand Sanitizer

Active Ingredients

Ethyl Alcohol 70% v/v

Purpose

Antiseptic

Uses:

Hand sanitizer to help bacteria on the skin.

For use when soap and water are not available.

Warnings

For external use only. Flammable. Keep away from fire or flame.

Do Not use

- On open skin wounds

When using this product keep out of eyes, ears, and mouth, in case of contact with eyes, rinse eyes thoroughly with water.

Stop use and ask a doctor if irritation or rash occurs. These may be signs of a serious condition.

Keep out of reach of children. If swallowed, get medical help or contact a Poison Control Center right away.

Directions

- Place enough product on hands to cover all surfaces. Rub hands together until dry.
- Supervise children under 6 years of age when using this product to avoid swallowing.

Other information

- Store below 110F (43C)
- May discolor fabrics or surfaces

Inactive ingredients

Water, Glycerin, Carbomer, Perfume, Triethanolamine, Tocopheryl Acetate, Aloe Barbadensis Leaf Juice

Questions

P: +1 703 343 67 67

Mon -Fri 9:00 AM-5:00 PM You may also report serious side effects to this phone number.

Moisturizing with vitamin E and Aloe

KILLS 99% OF VIRUSES & GERMS

Distributed by:

Asena's Group LLC 22102 VA

www.asenasgroup.com

info@asenasgroup.com

Made in TURKEY